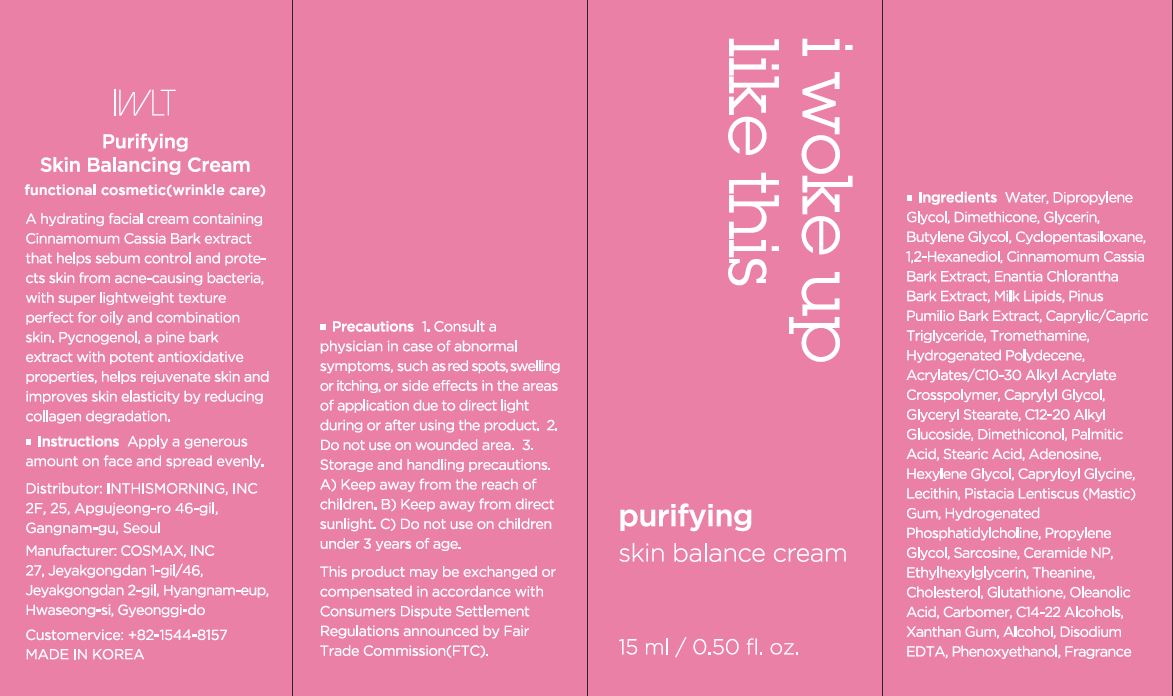 DRUG LABEL: Puritying Skin BalanceCream
NDC: 71217-0052 | Form: CREAM
Manufacturer: inthismorning co ltd
Category: otc | Type: HUMAN OTC DRUG LABEL
Date: 20230129

ACTIVE INGREDIENTS: .ALPHA.-HEXYLCINNAMALDEHYDE 0.00244785 g/100 mL; LIMONENE, (+)- 0.001156785 g/100 mL
INACTIVE INGREDIENTS: WATER; GLYCERIN

Drug Facts

ACTIVE INGREDIENT

Hexyl Cinnamal, limonene

INACTIVE INGREDIENT

Water
Dipropylene Glycol
Glycerin
Dimethicone
Butylene Glycol
Cyclopentasiloxane
1,2-Hexanediol
Tromethamine
Carbomer
Caprylic/Capric Triglyceride
C14-22 Alcohols
Hydrogenated Polydecene
Acrylates/C10-30 Alkyl Acrylate Crosspolymer
Caprylyl Glycol
Glyceryl Stearate
C12-20 Alkyl Glucoside
Dimethiconol
Palmitic Acid
Ethylhexylglycerin
Stearic Acid
Adenosine
Fragrance(Parfum)
Disodium EDTA
Xanthan Gum
Biosaccharide Gum-1
Pyrus Malus (Apple) Fruit Extract
Maltodextrin
Saccharide Hydrolysate
Hamamelis Virginiana (Witch Hazel) Water
Tocopherol
Pistacia Lentiscus (Mastic) Gum
Hydrogenated Lecithin
Spiraea Ulmaria Extract
Phenethyl Alcohol

PURPOSE

wrinkle care

keep out or reach of the children

INDICATIONS AND USAGE

apply a generous amount on face and spread evenly

WARNINGS

This product is for exeternal use only. Do not use for internal use
Storage and handling precautions
If possible, avoid direct sunlight and store in cool and area of low humidity in order to maintain the quality of the product and avoid misuse
Avoid placing the product near fire and store out in reach of children

- consult a physician in case of abnormal symptoms, such as red spots, swelling or itching, or side effects in the areas of application due to direct light during or after using the product

- do not use on wounded area

DOSAGE AND ADMINISTRATION

for external use only